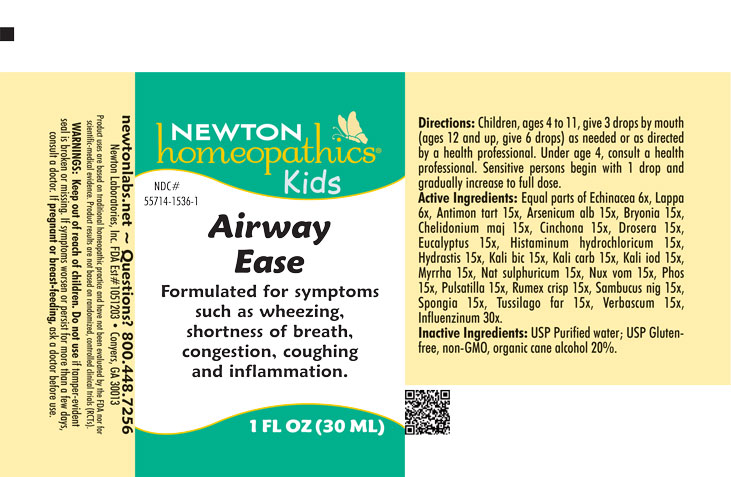 DRUG LABEL: Airway Ease
NDC: 55714-1536 | Form: LIQUID
Manufacturer: Newton Laboratories, Inc.
Category: homeopathic | Type: HUMAN OTC DRUG LABEL
Date: 20250507

ACTIVE INGREDIENTS: SPONGIA OFFICINALIS SKELETON, ROASTED 15 [hp_X]/1 mL; TUSSILAGO FARFARA 15 [hp_X]/1 mL; VERBASCUM THAPSUS 15 [hp_X]/1 mL; ECHINACEA, UNSPECIFIED 6 [hp_X]/1 mL; ARCTIUM LAPPA ROOT 6 [hp_X]/1 mL; INFLUENZA B VIRUS 30 [hp_X]/1 mL; INFLUENZA A VIRUS 30 [hp_X]/1 mL; ANTIMONY POTASSIUM TARTRATE 15 [hp_X]/1 mL; ARSENIC TRIOXIDE 15 [hp_X]/1 mL; BRYONIA ALBA ROOT 15 [hp_X]/1 mL; CHELIDONIUM MAJUS 15 [hp_X]/1 mL; CINCHONA OFFICINALIS BARK 15 [hp_X]/1 mL; DROSERA ANGLICA 15 [hp_X]/1 mL; EUCALYPTUS GUM 15 [hp_X]/1 mL; HISTAMINE DIHYDROCHLORIDE 15 [hp_X]/1 mL; GOLDENSEAL 15 [hp_X]/1 mL; POTASSIUM DICHROMATE 15 [hp_X]/1 mL; POTASSIUM CARBONATE 15 [hp_X]/1 mL; POTASSIUM IODIDE 15 [hp_X]/1 mL; MYRRH 15 [hp_X]/1 mL; SODIUM SULFATE 15 [hp_X]/1 mL; STRYCHNOS NUX-VOMICA SEED 15 [hp_X]/1 mL; PHOSPHORUS 15 [hp_X]/1 mL; ANEMONE PULSATILLA 15 [hp_X]/1 mL; RUMEX CRISPUS ROOT 15 [hp_X]/1 mL; SAMBUCUS NIGRA FLOWERING TOP 15 [hp_X]/1 mL
INACTIVE INGREDIENTS: WATER; ALCOHOL

Airway 1536L

OTC - KEEP OUT OF REACH OF CHILDREN SECTION

Keep out of reach of children.

OTC - PREGNANCY OR BREAST FEEDING SECTION

If pregnant or breast-feeding, ask a doctor before use.

WARNINGS SECTION

Warning:Keep out of reach of children. Do not use if tamper - evident seal is broken or missing. If symptoms worsen or persist for more than a few days, consult a doctor. If pregnant or breast-feeding, ask a doctor before use.

QUESTIONS SECTION

newtonlabs.net – Questions? 800.448.7256

Newton Laboratories, Inc. FDA Est # 1051203 - Conyers, GA 30013

INACTIVE INGREDIENT SECTION

Inactive Ingredients: USP Purified Water; USP Gluten-free, non-GMO, organic cane alcohol 20%

OTC - PURPOSE SECTION

Formulated for symptoms such as wheezing, shortness of breath, congestion, coughing, and inflammation.

OTC - ACTIVE INGREDIENT SECTION

Equal parts of Echinacea 6x, Lappa 6x, Antimon. tart. 15x, Arsenicum alb. 15x, Bryonia 15x, Chelidonium maj.15x, Cinchona 15x, Drosera 15x, Eucalyptus 15x, Histaminum hydrochloricum 15x, Hydrastis 15x, Kali bic. 15x, Kali carb. 15x, Kali iod. 15x, Myrrha 15x, Nat. sulphuricum 15x, Nux vom. 15x, Phos. 15x, Pulsatilla 15x, Rumex crisp. 15x, Sambucus nig. 15x, Spongia 15x, Tussilago far. 15x, Verbascum 15x, Influenzinum 30x.

DOSAGE & ADMINISTRATION SECTION

Directions: Children, ages 4 to 11, give 3 drops by mouth (ages 12 and up, give 6 drops) as needed or as directed by a health professional. Under age 4, consult a health professional. Sensitive persons begin with 1 drop and gradually increase to full dose.

INDICATIONS & USAGE SECTION

Formulated for symptoms such as wheezing, shortness of breath, congestion, coughing, and inflammation.